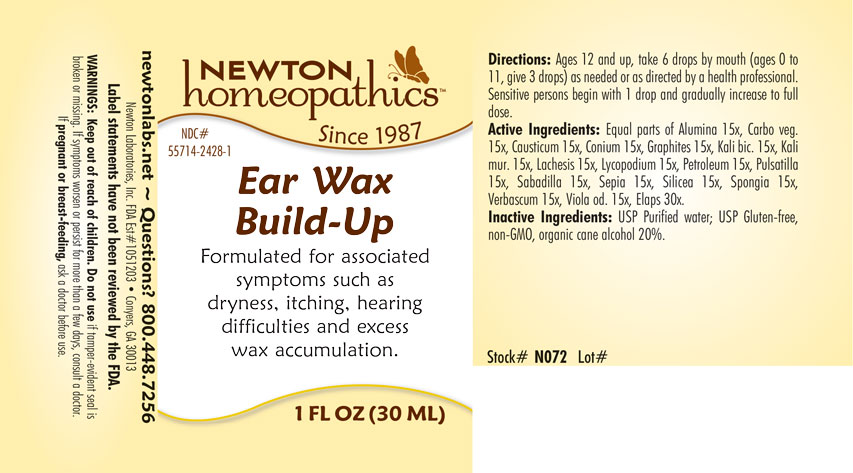 DRUG LABEL: Ear Wax Build-Up
NDC: 55714-2428 | Form: LIQUID
Manufacturer: Newton Laboratories, Inc.
Category: homeopathic | Type: HUMAN OTC DRUG LABEL
Date: 20250206

ACTIVE INGREDIENTS: MICRURUS CORALLINUS VENOM 30 [hp_X]/1 mL; ALUMINUM OXIDE 15 [hp_X]/1 mL; ACTIVATED CHARCOAL 15 [hp_X]/1 mL; CAUSTICUM 15 [hp_X]/1 mL; CONIUM MACULATUM FLOWERING TOP 15 [hp_X]/1 mL; GRAPHITE 15 [hp_X]/1 mL; POTASSIUM DICHROMATE 15 [hp_X]/1 mL; POTASSIUM CHLORIDE 15 [hp_X]/1 mL; LACHESIS MUTA VENOM 15 [hp_X]/1 mL; LYCOPODIUM CLAVATUM SPORE 15 [hp_X]/1 mL; LIQUID PETROLEUM 15 [hp_X]/1 mL; PULSATILLA VULGARIS 15 [hp_X]/1 mL; SCHOENOCAULON OFFICINALE SEED 15 [hp_X]/1 mL; SEPIA OFFICINALIS JUICE 15 [hp_X]/1 mL; SILICON DIOXIDE 15 [hp_X]/1 mL; SPONGIA OFFICINALIS SKELETON, ROASTED 15 [hp_X]/1 mL; VERBASCUM THAPSUS 15 [hp_X]/1 mL; VIOLA ODORATA 15 [hp_X]/1 mL
INACTIVE INGREDIENTS: ALCOHOL; WATER

EarWa 2428L

INDICATIONS & USAGE SECTION

Formulated for associated symptoms such as dryness, itching, hearing difficulties and excess wax accumulation.

DOSAGE & ADMINISTRATION SECTION

Directions: Ages 12 and up, take 6 drops by mouth (ages 0 to 11, give 3 drops) as needed or as directed by a health professional. Sensitive persons begin with 1 drop and gradually increase to full dose.

OTC - ACTIVE INGREDIENT SECTION

Equal parats of Alumina 15x, Carbo veg. 15x, Causticum 15x, Conium 15x, Graphites 15x, Kali bic. 15x, Kali mur. 15x, Lachesis 15x, Lycopodium 15x, Petroleum 15x, Pulsatilla 15x, Sabadilla 15x, Sepia 15x, Silicea 15x, Spongia 15x, Verbascum 15x, Viola odorata 15x, Elaps 30x.

OTC - PURPOSE SECTION

Formulated for associated symptoms such as dryness, itching, hearing difficulties and excess wax accumulation.

INACTIVE INGREDIENT SECTION

Inactive Ingredients: USP Purified Water; USP Gluten-free, non-GMO, organic cane alcohol 20%.

QUESTIONS SECTION

newtonlabs.net - Questions? 800.448.7256

Newton Laboratories, Inc. FDA Est # 1051203 - Conyers, GA 30013

WARNINGS SECTION

WARNINGS: Keep out of reach of children. Do not use if tamper-evident seal is broken or missing. If symptoms or persist for more than a few days, consult a doctor. If pregnant or breast-feeding, ask a doctor before use.

OTC - PREGNANCY OR BREAST FEEDING SECTION

If pregnant or breast-feeding, ask a doctor before use.

OTC - KEEP OUT OF REACH OF CHILDREN SECTION

Keep out of reach of children.